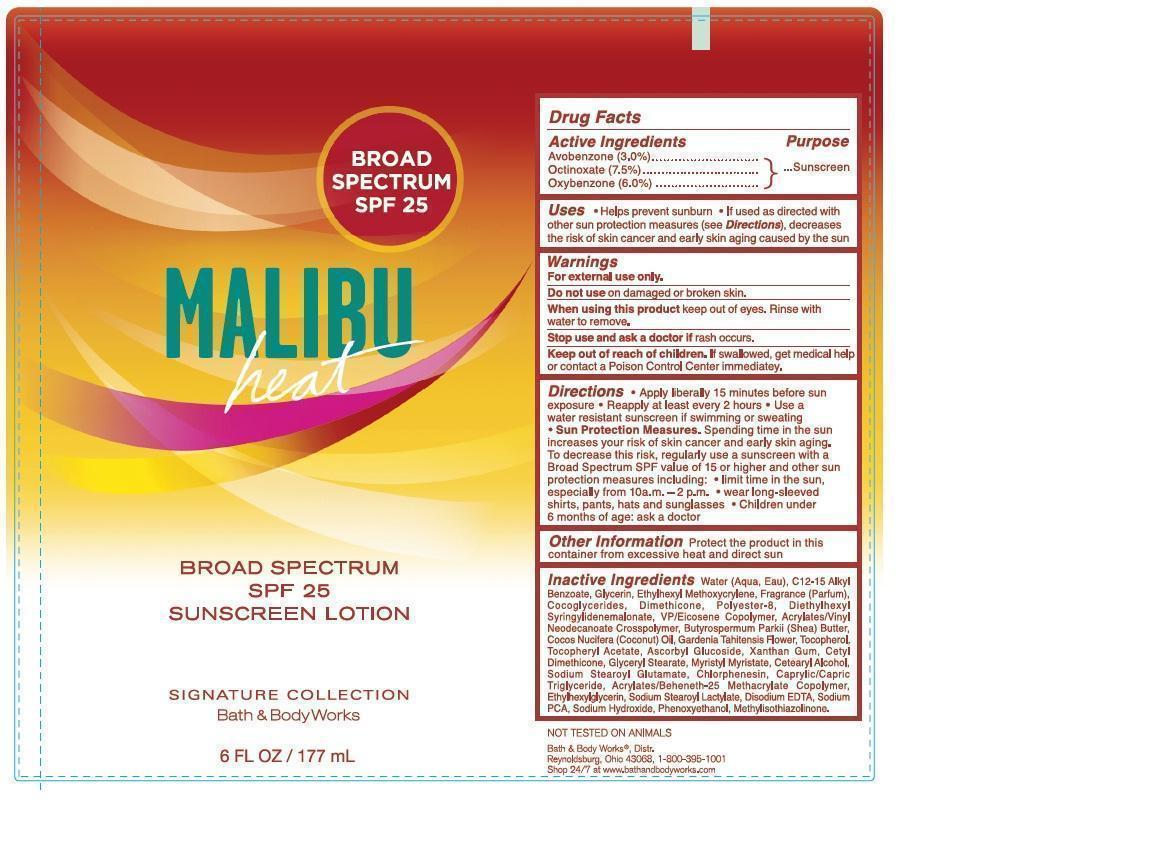 DRUG LABEL: Signature Sunscreen Broad Spectrum SPF 25 Malibu Heat
NDC: 62670-8045 | Form: LOTION
Manufacturer: Bath & Body Works, Inc.
Category: otc | Type: HUMAN OTC DRUG LABEL
Date: 20130909

ACTIVE INGREDIENTS: AVOBENZONE 3.0 g/100 mL; OCTINOXATE 7.5 g/100 mL; OXYBENZONE 6.0 g/100 mL
INACTIVE INGREDIENTS: WATER

ACTIVE INGREDIENTS

Avobenzone 3.0%, Octinoxate 7.5%, Oxybenzone 6.0%

PURPOSE

Sunscreen

USES

- Helps prevent sunburn
- If used as directed with other sun protection measures (see Directions), decreases the risk of skin cancer and early skin aging caused by the sun

WARNINGS

For external use only.

DO NOT USE

on damaged or broken skin.

WHEN USING THIS PRODUCT

keep out of eyes. Rinse with water to remove.

STOP USE AND ASK A DOCTOR IF

rash occurs.

KEEP OUT OF REACH OF CHILDREN.

If swallowed, get medical help or contact a Poison Control Center immediately.

DIRECTIONS

- Apply liberally 15 minutes before sun exposure
- Reapply at least every 2 hours
- Use a water resistant sunscreen if swimming or sweating
- Sun Protection Measures. Spending time in the sun increases your risk of skin cancer and early skin aging. To decrease this risk, regularly use a sunscreen with a Broad Spectrum SPF value of 15 or higher and other sun protection measures including:
- limit time in the sun, especially from 10 a.m. - 2 p.m.
- wear long-sleeved shirts, pants, hats and sunglasses
- children under 6 months of age: ask a doctor

OTHER INFORMATION

Protect the product in this container from excessive heat and direct sun.

INACTIVE INGREDIENTS

Water (Aqua, Eau), C12-15 Alkyl Benzoate, Glycerin, Ethylhexyl Methoxycrylene, Fragrance (Parfum), Cocoglycerides, Dimethicone, Polyester-8, Diethylhexyl Syringylidenemalonate, VP/Eicosene Copolymer, Acrylates/Vinyl Neodecanoate Crosspolymer, Butyrospermum Parkii (Shea) Butter, Cocos Nucifera (Coconut) Oil, Gardenia Tahitensis Flower, Tocopherol, Tocopheryl Acetate, Ascorbyl Glucoside, Xanthan Gum, Cetyl Dimethicone, Glyceryl Stearate, Myristyl Myristate, Cetearyl Alcohol, Sodium Stearoyl Glutamate, Chlorphenesin, Caprylic/Capric Triglyceride, Acrylates/Beheneth-25 Methacrylate Copolymer, Ethylhexylglycerin, Sodium Stearoyl Lactylate, Disodium EDTA, Sodium PCA, Sodium Hydroxide, Phenoxyethanol, Methylisothiazolinone.

COMPANY INFORMATION

Bath & Body Works, Distr.

Reynoldsburg, Ohio 43068

1-800-395-1001

www.bathandbodyworks.com